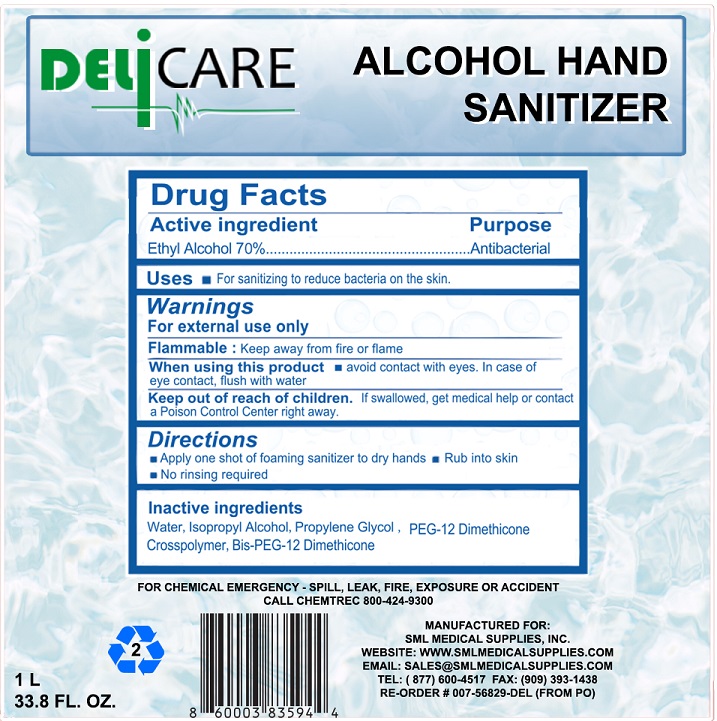 DRUG LABEL: ALCOHOL HAND SANITIZER
NDC: 76591-103 | Form: SOLUTION
Manufacturer: Guangzhou Gotdya Fine Chemical Co., Ltd.
Category: otc | Type: HUMAN OTC DRUG LABEL
Date: 20210308

ACTIVE INGREDIENTS: ALCOHOL 70 mL/100 mL
INACTIVE INGREDIENTS: WATER; ISOPROPYL ALCOHOL; PROPYLENE GLYCOL; PEG-12 DIMETHICONE (300 CST); BIS-PEG-12 DIMETHICONE (70 MPA.S)

Delicare Alcohol Hand Sanitizer (Item#007-56829-DEL), 70% Ethyl Alcohol

Active ingredient

Ethyl Alcohol 70 %

PURPOSE

ANTIBACTERIAL

Uses

- FOR SANITIZING TO REDUCE BACTERIA ON THE SKIN.

Warnings

FOR EXTERNAL USE ONLY

FLAMMABLE : KEEP AWAY FROM FIRE OR FLAME

WHEN USING THIS PRODUCT

- AVOID CONTACT WITH EYES, IN CASE OF EYE CONTACT, FLUSH WITH WATER.

KEEP OUT OF REACH OF CHILDREN. IF SWALLOWED, GET MEDICAL HELP OR CONTACT A POISON CONTROL CENTER RIGHT AWAY.

Directions

- APPLY ONE SHOT OF FOAMING SANITIZER TO DRY HANDS
- RUB INTO SKIN
- NO RINSING REQUIRED

Inactive ingredients

WATER, ISOPROPYL ALCOHOL, PROPYLENE GLYCOL, PEG-12 DIMETHICONE CROSSPOLYMER, BIS-PEG-12 DIMETHICONE